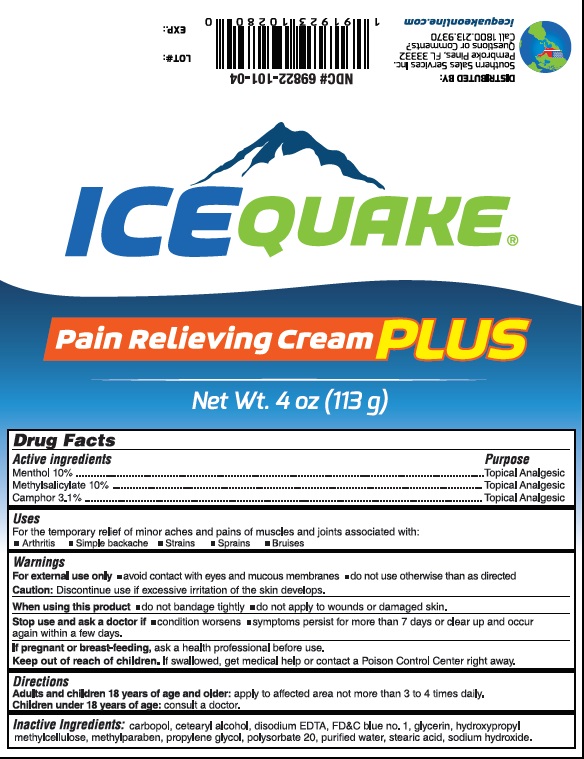 DRUG LABEL: Ice Quake
NDC: 69822-101 | Form: CREAM
Manufacturer: Southern Sales & Service, Inc.
Category: otc | Type: HUMAN OTC DRUG LABEL
Date: 20170105

ACTIVE INGREDIENTS: MENTHOL 10 g/100 g; METHYL SALICYLATE 10 g/100 g; CAMPHOR (SYNTHETIC) 3.1 g/100 g
INACTIVE INGREDIENTS: HYPROMELLOSE 2910 (10000 MPA.S); GLYCERIN; FD&C BLUE NO. 1; CARBOMER HOMOPOLYMER TYPE A (ALLYL PENTAERYTHRITOL CROSSLINKED); ISOPROPYL ALCOHOL; PROPYLENE GLYCOL; METHYLPARABEN; SODIUM HYDROXIDE; WATER

Active Ingredients Purpose

Methyl Salicylate 10% Topical Analgesic

Menthol 10% Topical Analgesic

Camphor 3.1% Topical Analgesic

Purpose

Topical Analgesic

Uses

temporarily relieves minor pain associated with

- Arthritis
- Smple backache
- Strains
- Bruises
- Pprains
- Cramps

Warnings

For external use only

IF MEDICINE COMES IN CONTACT WITH HANDS, WASH WITH SOAP AND WATER

Stop use and ask a doctor if

- condition worsens
- redness is present
- irritation develops

When using this product:

- Use only as directed
- Do not bandage tightly
- Do not use with a heating devices
- Avoid contact with the eyes and mucous membranes
- Do not apply to wounds, damaged, broken or irritated skin
- If severe burning sensation occurs, discontinue use immediately
- Do not expose the area treated with product to heat or direct sunlight

Keep out of reach of children.

If swallowed get medical help or contact a Poison Control Center right away.

Directions

- adults and children over 18 years and older:
- Apply to affected area
- Squeeze desired amount of IceQuake Plus onto affected area
- massage dispensed cream into painful area until thoroughly absorbed
- Repeat as necessary, but no more than 3 to 4 times daily

INACTIVE INGREDIENT

Inactive ingredients: HPMC, glycerin, FD&C Blue No.1, carbopol, isopropyl alcohol, propylene glycol, methylparaben, sodium hydroxide, water

DISTRIBUTE BY:

SSS Group, LLC Pembroke Pines, Fl 33332

Questions or Comments?

Call 1 800.213.9370